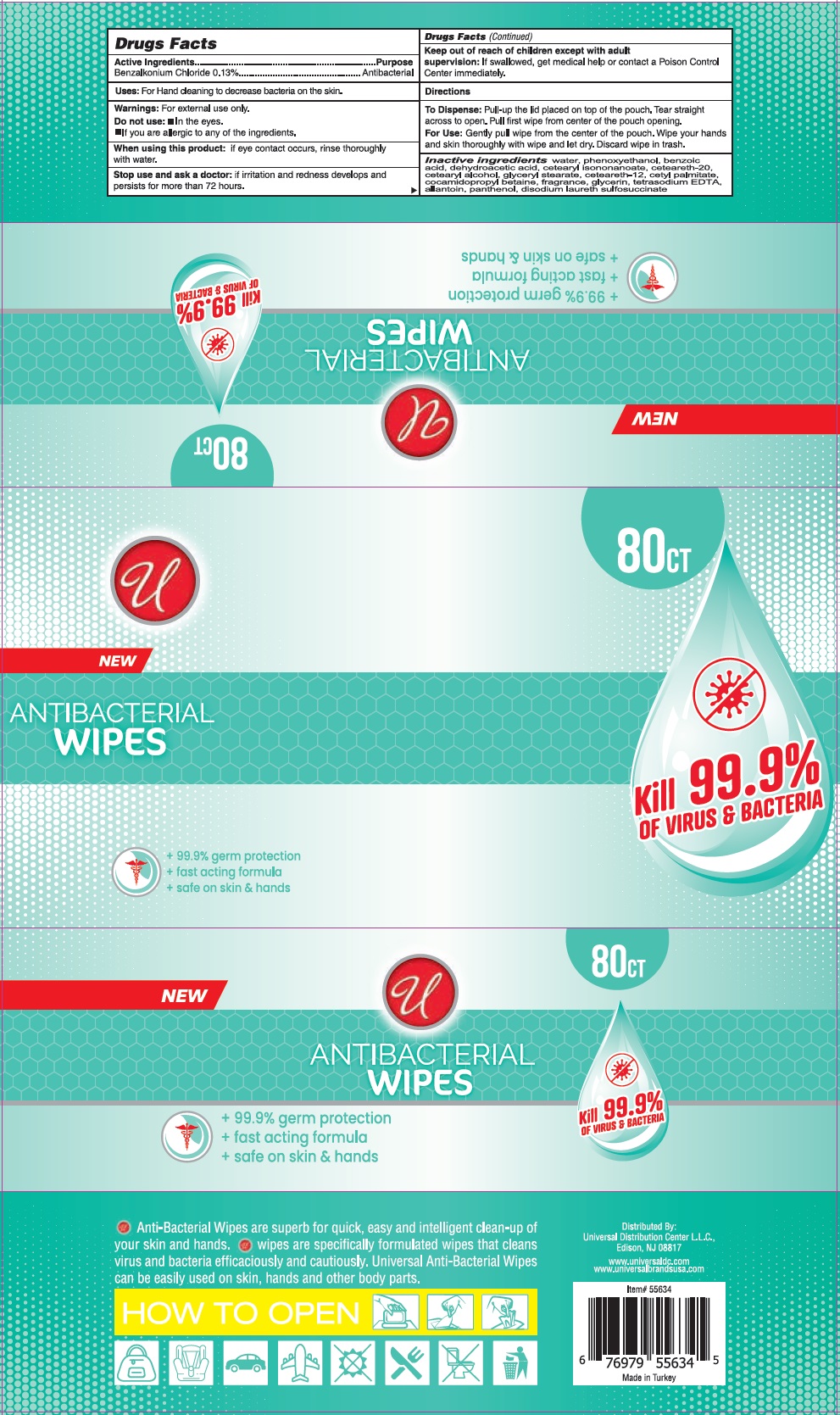 DRUG LABEL: UNIVERSAL ANTIBACTERIAL WIPES
NDC: 79761-101 | Form: CLOTH
Manufacturer: Monna Kimya Ve Kozmetik Sanayi Ticaret Limited Sirketi
Category: otc | Type: HUMAN OTC DRUG LABEL
Date: 20200725

ACTIVE INGREDIENTS: BENZALKONIUM CHLORIDE 0.13 g/100 mL
INACTIVE INGREDIENTS: WATER; PHENOXYETHANOL; BENZOIC ACID; DEHYDROACETIC ACID; CETEARYL ISONONANOATE; POLYOXYL 20 CETOSTEARYL ETHER; CETOSTEARYL ALCOHOL; GLYCERYL MONOSTEARATE; CETEARETH-12; CETYL PALMITATE; COCAMIDOPROPYL BETAINE; GLYCERIN; EDETATE SODIUM; ALLANTOIN; PANTHENOL; DISODIUM LAURETH SULFOSUCCINATE

U ANTIBACTERIAL WIPES

Active Ingredients

Benzalkonium Chloride 0.13%

Purpose

Antibacterial

INDICATIONS AND USAGE

Uses: For Hand cleaning to decrease bacteria on the skin.

Warnings: For external use only.

Do not use: ▪ In the eyes.

▪ If you are allergic to any of the ingredients.

When using this product: if eye contact occurs, rinse thoroughly with water.

Stop use and ask a doctor: if irritation and redness develops and persists for more than 72 hours.

Keep out of reach of children except with adult supervision: If swallowed get medical help or contact a Poison Control Center immediately.

Directions

To Dispense: Pull-up the lid placed on top of the pouch. Tear straight across to open. Pull first wipe from center of the pouch opening.

For use: Gently pull wipe from the center of the pouch. Wipe your hands and skin thoroughly with wipe and let dry. Discard wipe in trash.

INACTIVE INGREDIENT

Inactive ingredients water, Phenoxyethanol, benzoic acid, dehydroacetic acid, cetearyl isononanoate, ceteareth-20, cetearyl alcohol, glyceryl stearate, ceteareth-12, cetyl palmitate, cocamidopropyl betaine, fragrance, glycerin, tetrasodium EDTA, allantoin, panthenol, disodium laureth sulfosuccinate

NEW

ANTIBACTERIAL WIPES

Kill 99.9% OF VIRUS & BACTERIA

+ 99.9% germ protection

+ fast acting formula

+ safe on skin & hands

• Anti-Bacterial Wipes are superb for quick, easy and intelligent clean-up of your skin and hands. • wipes are specifically formulated wipes that cleans virus and bacteria efficaciously and cautiously. Universal Anti-Bacterial Wipes can be easily used on skin, hands and other body parts.

Distributed By:

Univeral Distribution Center L.L.C.,

Edison, NJ 08817

www.universaldc.com

www.universalbrandsusa.com

Made in Turkey